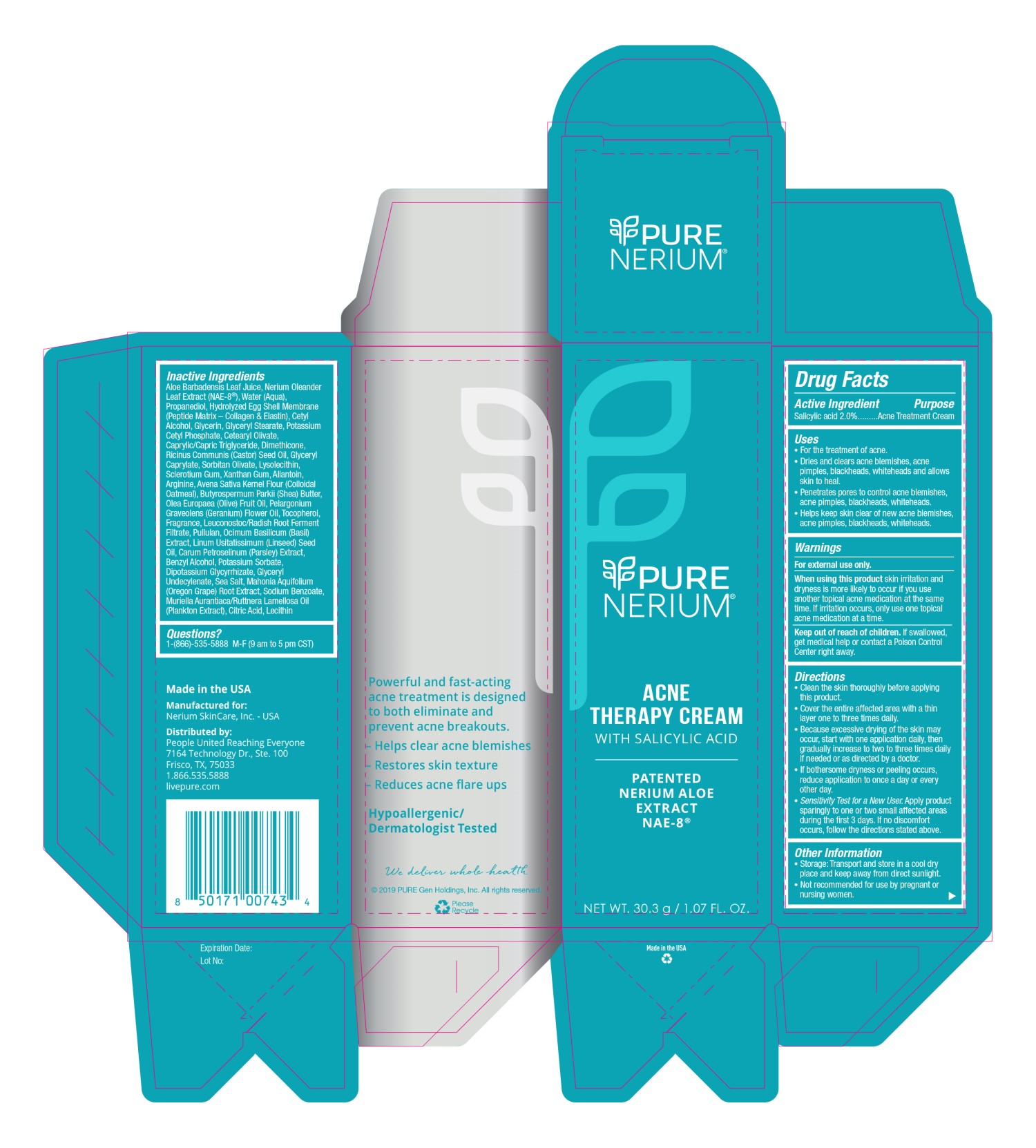 DRUG LABEL: PURE NERIUM ACNE THERAPY
NDC: 72216-227 | Form: CREAM
Manufacturer: Nerium SkinCare, Inc.
Category: otc | Type: HUMAN OTC DRUG LABEL
Date: 20191003

ACTIVE INGREDIENTS: SALICYLIC ACID 2 g/100 g
INACTIVE INGREDIENTS: MEDIUM-CHAIN TRIGLYCERIDES; GLYCERYL 1-UNDECYLENATE; PULLULAN; GLYCYRRHIZINATE DIPOTASSIUM; LEUCONOSTOC/RADISH ROOT FERMENT FILTRATE; NERIUM OLEANDER LEAF; WATER; BETASIZOFIRAN; XANTHAN GUM; OATMEAL; SHEA BUTTER; TOCOPHEROL; EGG SHELL MEMBRANE; GLYCERYL STEARATE SE; PELARGONIUM GRAVEOLENS FLOWER OIL; CETYL ALCOHOL; GLYCERIN; POTASSIUM CETYL PHOSPHATE; CETEARYL OLIVATE; RICINUS COMMUNIS SEED; GLYCERYL CAPRYLATE; ANHYDROUS CITRIC ACID; SODIUM BENZOATE; MAHONIA AQUIFOLIUM ROOT; LECITHIN, SOYBEAN; OCIMUM BASILICUM WHOLE; PROPANEDIOL; LINSEED OIL; PARSLEY; BENZYL ALCOHOL; POTASSIUM SORBATE; SEA SALT; DIMETHICONE; SORBITAN OLIVATE; LYSOPHOSPHATIDYLCHOLINE, SOYBEAN; ALLANTOIN; ARGININE; OLIVE OIL; ALOE VERA LEAF

PURE NERIUM ACNE THERAPY CREAM

PURPOSE

Acne Treatment Cream

ACTIVE INGREDIENT

Salicylic acid 2.0%.

INDICATIONS AND USAGE

• For the treatment of acne.
• Dries and clears acne blemishes, acne pimples, blackheads, whiteheads and allows skin to heal.
• Penetrates pores to control acne blemishes, acne pimples, blackheads, whiteheads.
• Helps keep skin clear of new acne blemishes, acne pimples, blackheads, whiteheads.

WARNINGS

For external use only.

When using this product skin irritation and dryness is more likely to occur if you use another topical acne medication at the same time. If irritation occurs, only use one topical acne medication at a time.

KEEP OUT OF REACH OF CHILDREN

If swallowed, get medical help or contact a Poison Control Center right away.

INSTRUCTIONS FOR USE

• Clean the skin thoroughly before applying this product.
• Cover the entire affected area with a thin layer one to three times daily.
• Because excessive drying of the skin may occur, start with one application daily, then gradually increase to two to three times daily if needed or as directed by a doctor.
• If bothersome dryness or peeling occurs, reduce application to once a day or every other day.
• Sensitivity Test for a New User. Apply product sparingly to one or two small affected ares during the first 3 days. If no discomfort occurs, follow the directions stated above.

OTHER SAFETY INFORMATION

Not recommended for use by pregnant or nursing women.

STORAGE AND HANDLING

Transport and store in a cool dry place and keep away from direct sunlight.

INACTIVE INGREDIENT

Aloe Barbadensis Leaf Juice, Nerium Oleander Leaf Extract (NAE8®), Water (Aqua), Propanediol, Hydrolyzed Egg Shell Membrane (Peptide Matrix – Collagen & Elastin), Cetyl Alcohol, Glycerin, Glyceryl Stearate, Potassium Cetyl Phosphate, Cetearyl Olivate, Caprylic/Capric Triglyceride, Dimethicone, Ricinus Communis (Castor) Seed Oil, Glyceryl Caprylate, Sorbitan Olivate, Lysolecithin, Sclerotium Gum, Xanthan Gum, Allantoin, Arginine, Avena Sativa Kernel Flour (Colloidal Oatmeal), Butyrospermum Parkii (Shea) Butter, Olea Europaea (Olive) Fruit Oil, Pelargonium Graveolens (Geranium) Flower Oil, Tocopherol, Fragrance, Leuconostoc/Radish Root Ferment Filtrate, Pullulan, Ocimum Basilicum (Basil) Extract, Linum Usitatissimum (Linseed) Seed Oil, Carum Petroselinum (Parsley) Extract, Benzyl Alcohol, Potassium Sorbate, Dipotassium Glycyrrhizate, Glyceryl Undecylenate, Sea Salt, Mahonia Aquifolium (Oregon Grape) Root Extract, Sodium Benzoate, Muriella Aurantiaca/Ruttnera Lamellosa Oil (Plankton Extract), Citric Acid, Lecithin

QUESTIONS

1-(844)-599-7787 M-F (9 am to 5 pm CST)

DOSAGE AND ADMINISTRATION

2% Topical Cream

Principal Display Panel

PURE
NERIUM®

ACNE
THERAPY CREAM
WITH SALICYLIC ACID
PATENTED
NERIUM ALOE
EXTRACT

NAE-8®